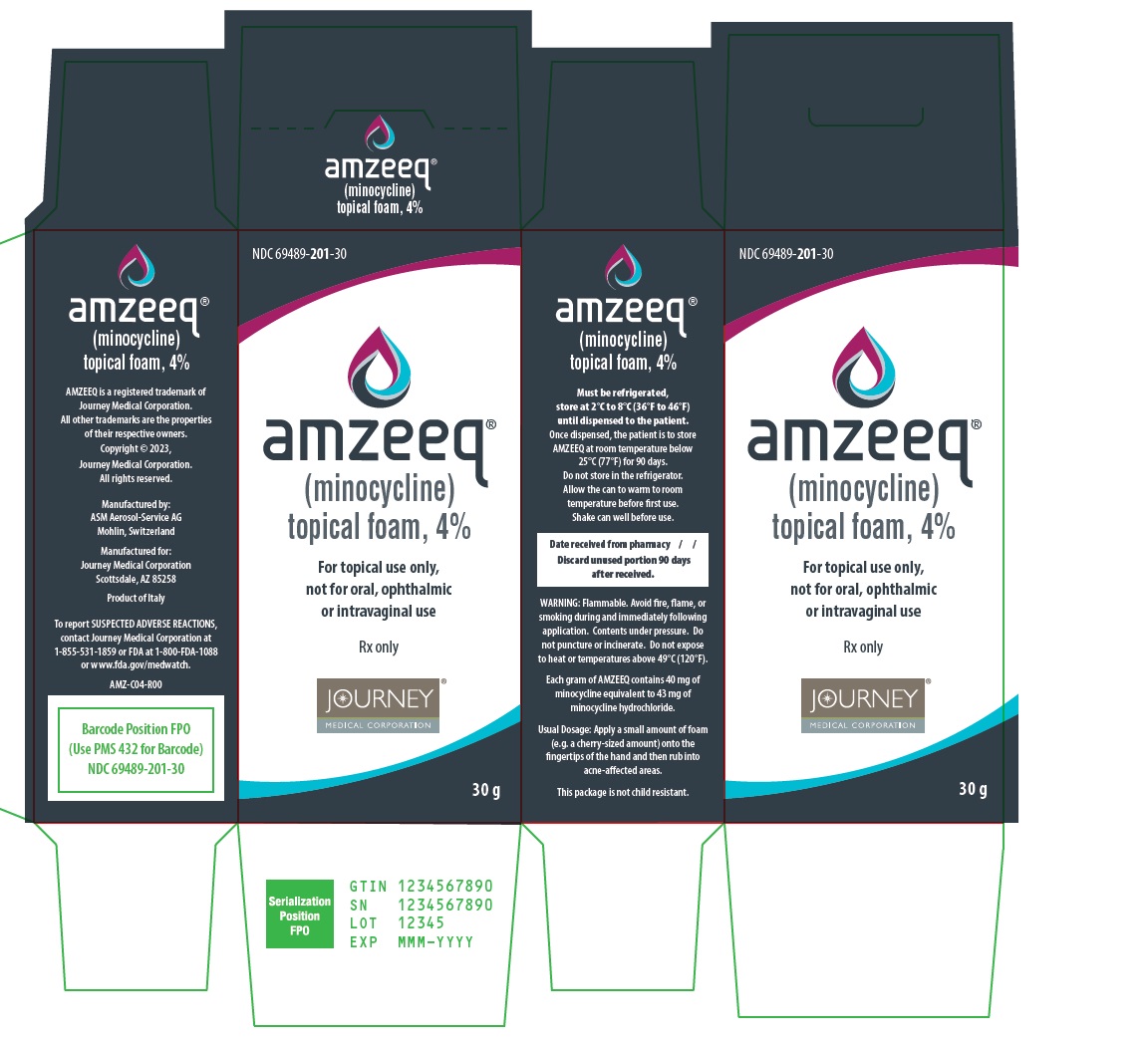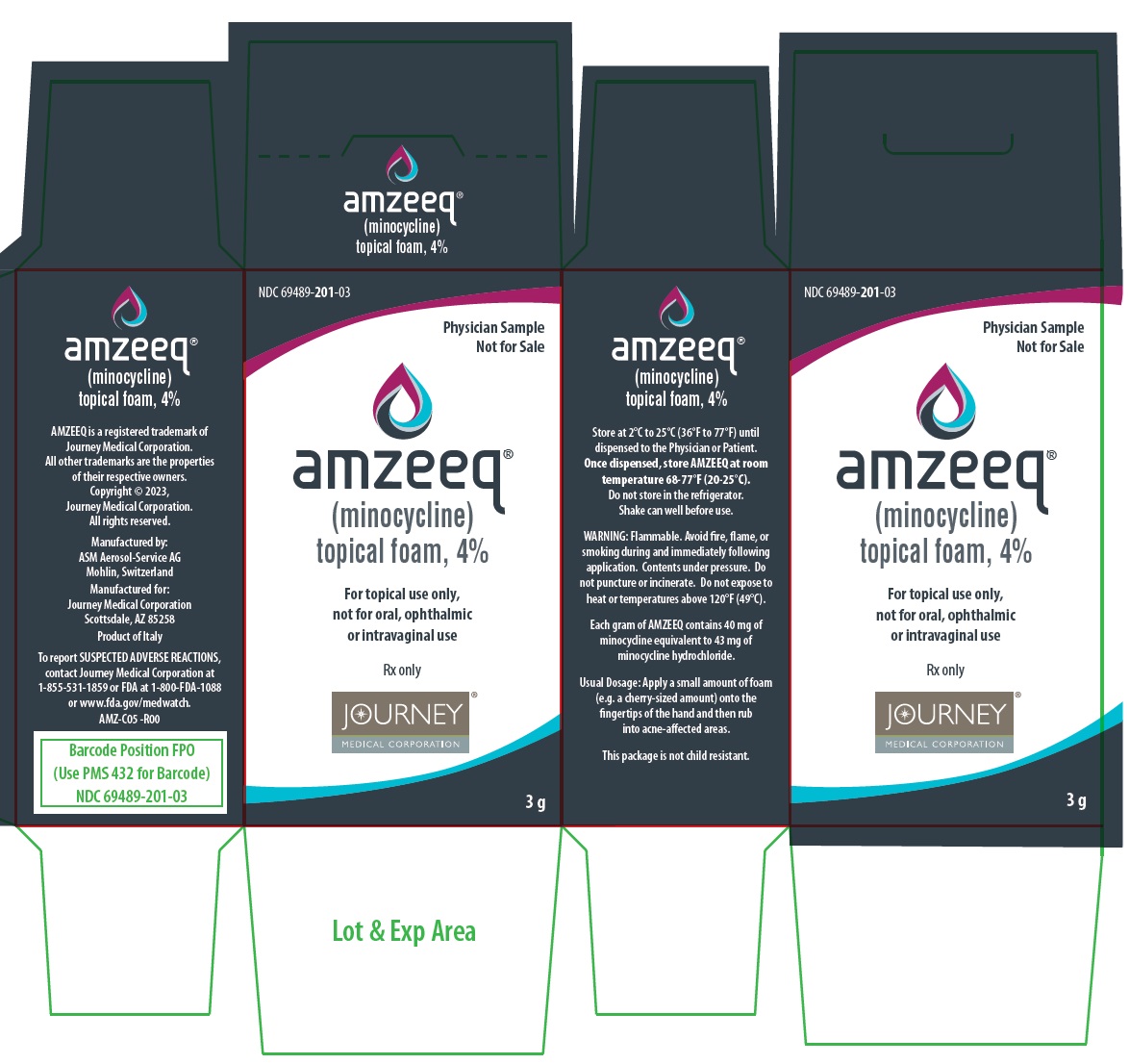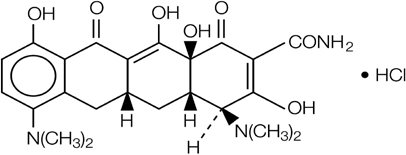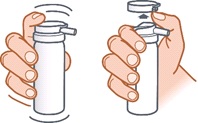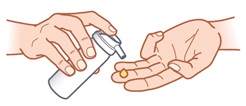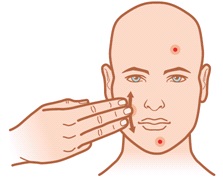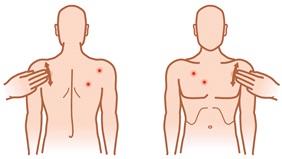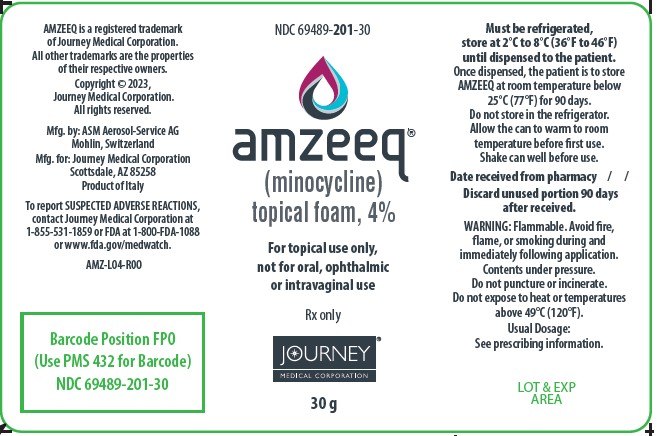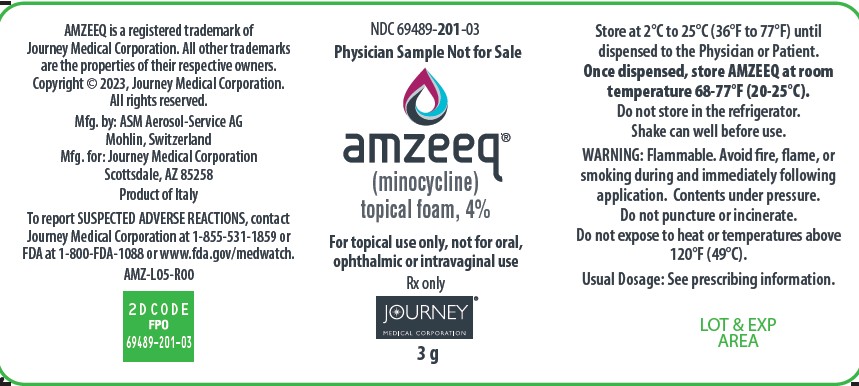 DRUG LABEL: AMZEEQ
NDC: 69489-201 | Form: AEROSOL, FOAM
Manufacturer: Journey Medical Corporation
Category: prescription | Type: HUMAN PRESCRIPTION DRUG LABEL
Date: 20231001

ACTIVE INGREDIENTS: MINOCYCLINE HYDROCHLORIDE 40 mg/1 g
INACTIVE INGREDIENTS: HYDROGENATED SOYBEAN OIL; COCONUT OIL; LIGHT MINERAL OIL; CYCLOMETHICONE; CETOSTEARYL ALCOHOL; STEARIC ACID; MYRISTYL ALCOHOL; HYDROGENATED CASTOR OIL; WHITE WAX; STEARYL ALCOHOL; DOCOSANOL; BUTANE; ISOBUTANE; PROPANE

HIGHLIGHTS OF PRESCRIBING INFORMATION

These highlights do not include all the information needed to use AMZEEQ safely and effectively. See full prescribing information for AMZEEQ.
AMZEEQ®(minocycline) topical foam
Initial U.S. Approval: 1971

1 INDICATIONS AND USAGE

AMZEEQ is a tetracycline-class drug indicated to treat inflammatory lesions of non-nodular moderate to severe acne vulgaris in patients 9 years of age and older. (1)
Limitations of Use

This formulation of minocycline has not been evaluated in the treatment of infections. To reduce the development of drug-resistant bacteria as well as to maintain the effectiveness of other antibacterial drugs, AMZEEQ should be used only as indicated. (5.14)

2 DOSAGE AND ADMINISTRATION

Apply AMZEEQ to affected areas once daily. AMZEEQ should be gently rubbed into the skin. (2)

3 DOSAGE FORMS AND STRENGTHS

Foam, 4% (3)

4 CONTRAINDICATIONS

This drug is contraindicated in persons who have shown hypersensitivity to any of the tetracyclines or any of the ingredients within AMZEEQ. (4)

5 WARNINGS AND PRECAUTIONS

- The propellant in AMZEEQ is flammable. Instruct the patient to avoid fire, flame, and smoking during and immediately following application. (5.1)
- The use of tetracycline-class of drugs orally during the second and third trimesters of pregnancy, infancy and childhood up to the age of 8 years may cause permanent discoloration of the teeth (yellow-gray-brown) and reversible inhibition of bone growth. (5.2, 5.3, 5.4, 8.1, 8.4)
- If Clostridioides difficileassociated diarrhea occurs, discontinue AMZEEQ. (5.5)
- If liver injury is suspected, discontinue AMZEEQ. (5.6)
- If renal impairment exists, oral minocycline doses may need to be adjusted to avoid excessive systemic accumulations of the drug and possible liver toxicity. (5.7)
- Oral minocycline may cause central nervous system side effects including lightheadedness, dizziness, or vertigo. (5.8)
- Oral minocycline may cause intracranial hypertension in adults and adolescents. Discontinue AMZEEQ if symptoms occur. (5.9)
- Oral minocycline has been associated with autoimmune syndromes; discontinue AMZEEQ immediately if symptoms occur. (5.10)
- Photosensitivity can occur with oral tetracycline. Patients should minimize or avoid exposure to natural or artificial sunlight. (5.11)
- Oral minocycline has been associated with anaphylaxis, serious skin reactions, erythema multiforme, and DRESS syndrome. Discontinue AMZEEQ immediately if symptoms occur. (5.12)

6 ADVERSE REACTIONS

The most commonly observed adverse reaction is headache. (6.1)

To report SUSPECTED ADVERSE REACTIONS, contact Journey Medical Corporation at 1-855-531-1859 or FDA at 1-800-FDA-1088 or www.fda.gov/medwatch.

7 DRUG INTERACTIONS

- Patients who are on anticoagulant therapy may require downward adjustment of their anticoagulant dosage. (7.1)
- Penicillin: avoid coadministration. (7.2)

8 USE IN SPECIFIC POPULATIONS

- Minocycline like other tetracycline-class drugs can cause fetal harm when administered orally to a pregnant woman. (5.2, 8.1)
- The use of drugs of the tetracycline class orally during tooth development may cause permanent discoloration of teeth. (5.3, 8.2, 8.4)
- Lactation: Breastfeeding not recommended. (8.2)

FULL PRESCRIBING INFORMATION

1 INDICATIONS AND USAGE

AMZEEQ is indicated for the topical treatment of inflammatory lesions of non-nodular moderate to severe acne vulgaris in adults and pediatric patients 9 years of age and older [ see Clinical Studies (14) ].

Limitations of Use

This formulation of minocycline has not been evaluated in the treatment of infections. To reduce the development of drug-resistant bacteria as well as to maintain the effectiveness of other antibacterial drugs, AMZEEQ should be used only as indicated [ see Warnings and Precautions (5.14) ].

2 DOSAGE AND ADMINISTRATION

For topical use only, not for oral, ophthalmic or intravaginal use [ see Clinical Studies (14) ].

After shaking the can well, a small amount of topical foam (e.g. a cherry-sized amount) should be expressed from the can onto the fingertips of the hand and then rubbed into acne-affected parts of the face. This should be repeated as needed until all acne-affected parts of the face are treated. If acne is present on other parts of the patient’s body (neck, shoulders, arms, back or chest), additional amounts of topical foam should also be applied to these areas. The topical foam should be applied at approximately the same time each day at least 1 hour before bedtime. The patient should not bathe, shower or swim for at least 1 hour after application of the product.

3 DOSAGE FORMS AND STRENGTHS

Topical foam, 4%

Each gram of AMZEEQ contains 40 mg of minocycline equivalent to 43 mg of minocycline hydrochloride and is supplied as a yellow suspension in a pressurized aluminum aerosol container (can).

4 CONTRAINDICATIONS

This drug is contraindicated in persons who have shown hypersensitivity to any of the tetracyclines or any other ingredients within AMZEEQ.

5 WARNINGS AND PRECAUTIONS

5.1 Flammability

The propellant in AMZEEQ is flammable. Instruct the patient to avoid fire, flame, and smoking during and immediately following application. Do not puncture and/or incinerate the containers. Do not expose containers to heat and/or store at temperatures above 120°F (49°C).

5.2 Teratogenic Effects

Minocycline, like other tetracycline-class drugs, may inhibit bone growth when administered orally during pregnancy. Based on animal data, when administered orally, tetracyclines cross the placenta, are found in fetal tissues, and can cause skeletal malformation and retardation of skeletal development on the developing fetus [see Use in Specific Populations (8.1) and Nonclinical Toxicology (13)] .

5.3 Tooth Discoloration

The use of tetracycline class drugs orally during tooth development (second and third trimesters of pregnancy, infancy, and childhood up to the age of 8 years) may cause permanent discoloration of the teeth (yellow-gray-brown). This adverse reaction is more common during long-term oral use of the tetracycline but has been observed following repeated short-term courses. Enamel hypoplasia has also been reported with oral tetracycline drugs. Use of tetracycline drugs is not recommended during tooth development.

The safety and effectiveness of AMZEEQ have not been established in pediatric patients less than 9 years of age.

5.4 Inhibition of Bone Growth

All tetracyclines form a stable calcium complex in any bone-forming tissue. A decrease in fibula growth rate has been observed in premature human infants given oral tetracycline in doses of 25 mg/kg every 6 hours. This reaction was shown to be reversible when the drug was discontinued. The safety and effectiveness of AMZEEQ have not been established in patients less than 9 years of age [see Use in Specific Populations (8.1, 8.4)].

Results of animal studies indicate that oral tetracyclines cross the placenta, are found in fetal tissues, and can cause retardation of skeletal development on the developing fetus. Evidence of embryotoxicity has been noted in animals treated orally early in pregnancy [see Use in Specific Populations (8.1)].

5.5 Clostridioides difficileAssociated Diarrhea

Clostridioides difficileassociated diarrhea (CDAD) has been reported with nearly all antibacterial agents, including oral minocycline, and may range in severity from mild diarrhea to fatal colitis. Treatment with antibacterial agents alters the normal flora of the colon leading to overgrowth of C. difficile.

C. difficileproduces toxins A and B which contribute to the development of CDAD. Hypertoxin producing strains of C. difficilecause increased morbidity and mortality, as these infections can be refractory to antimicrobial therapy and may require colectomy. CDAD must be considered in all patients who present with diarrhea following antibiotic use. Careful medical history is necessary since CDAD has been reported to occur over two months after the administration of antibacterial agents.

If CDAD is suspected or confirmed, antibiotic use not directed against C. difficilemay need to be discontinued. Appropriate fluid and electrolyte management, protein supplementation, antibiotic treatment of C. difficile, and surgical evaluation should be instituted as clinically indicated.

5.6 Hepatotoxicity

Post-marketing cases of serious liver injury, including irreversible drug-induced hepatitis and fulminant hepatic failure (sometimes fatal) have been reported with oral minocycline use in the treatment of acne.

5.7 Metabolic Effects

The anti-anabolic action of the tetracyclines may cause an increase in blood urea nitrogen (BUN). In patients with significantly impaired function, higher serum levels of tetracycline-class drugs may lead to azotemia, hyperphosphatemia, and acidosis. If renal impairment exists, recommended oral or parenteral doses may lead to excessive systemic accumulations of the drug and possible liver toxicity. Under such conditions, adjust the dose downward, and if therapy is prolonged, serum level determinations of the drug may be advisable.

5.8 Central Nervous System Effects

Central nervous system side effects including light-headedness, dizziness or vertigo have been reported with oral minocycline therapy. Patients who experience these symptoms should be cautioned about driving vehicles or using hazardous machinery while on minocycline therapy. These symptoms may disappear during therapy and may disappear when the drug is discontinued.

5.9 Intracranial Hypertension

Intracranial hypertension has been associated with the use of tetracycline-class drugs. Clinical manifestations of intracranial hypertension include headache, blurred vision, diplopia and vision loss; papilledema can be found on fundoscopy. Women of childbearing age who are overweight or have a history of IH are at a greater risk for developing intracranial hypertension. Patients should be questioned for visual disturbances prior to initiation of treatment with tetracyclines. Concomitant use of isotretinoin and tetracycline should be avoided because isotretinoin, a systemic retinoid, is also known to cause intracranial hypertension.

Although intracranial hypertension typically resolves after discontinuation of treatment, the possibility for permanent visual loss exists. If visual disturbance occurs during treatment, prompt ophthalmologic evaluation is warranted. Because intracranial pressure can remain elevated for weeks after drug cessation, patients should be monitored until they stabilize.

5.10 Autoimmune Syndromes

Tetracyclines have been associated with the development of autoimmune syndromes. The long-term use of oral minocycline in the treatment of acne has been associated with drug-induced lupus-like syndrome, autoimmune hepatitis and vasculitis. Sporadic cases of serum sickness have presented shortly after oral minocycline use. Symptoms may be manifested by fever, rash, arthralgia, and malaise. In symptomatic patients, immediately discontinue the use of all tetracycline-class drugs, including AMZEEQ.

5.11 Photosensitivity

Photosensitivity manifested by an exaggerated sunburn reaction has been observed in some individuals taking oral tetracyclines; this reaction has been reported less frequently with minocycline. Although AMZEEQ did not induce phototoxicity or photoallergic responses in human dermal safety studies, patients should minimize or avoid exposure to natural or artificial sunlight (tanning beds or UVA/B treatment) while using minocycline. If patients need to be outdoors while using AMZEEQ, they should wear loose-fitting clothes that protect skin from sun exposure and discuss other sun protection measures with their physician. Advise patients to discontinue treatment with AMZEEQ at the first evidence of sunburn.

5.12 Serious Skin/Hypersensitivity Reaction

Cases of anaphylaxis, serious skin reactions (e.g. Stevens Johnson syndrome), erythema multiforme, and drug reaction with eosinophilia and systemic symptoms (DRESS) syndrome have been reported postmarketing with oral minocycline use in patients with acne. DRESS syndrome consists of cutaneous reaction (such as rash or exfoliative dermatitis), eosinophilia, and one or more of the following visceral complications such as: hepatitis, pneumonitis, nephritis, myocarditis, and pericarditis. Fever and lymphadenopathy may be present. In some cases, death has been reported with oral minocycline use. If this syndrome is recognized, discontinue AMZEEQ immediately.

5.13 Tissue Hyperpigmentation

Oral tetracyclines are known to cause hyperpigmentation. Tetracycline therapy may induce hyperpigmentation in many organs, including nails, bone, skin, eyes, thyroid, visceral tissue, oral cavity (teeth, mucosa, alveolar bone), sclerae and heart valves. Skin and oral pigmentation has been reported to occur independently of time or amount of drug administration, whereas other tissue pigmentation has been reported to occur upon prolonged administration. Skin pigmentation includes diffuse pigmentation as well as pigmentation over sites of scars or injury.

5.14 Development of Drug-Resistant Bacteria

AMZEEQ has not been evaluated in the treatment of infections. Bacterial resistance to the tetracyclines may develop in patients using AMZEEQ, therefore, the susceptibility of bacteria associated with infection should be considered in selecting antimicrobial therapy. Because of the potential for drug-resistant bacteria to develop during the use of AMZEEQ, it should be used only as indicated.

5.15 Superinfection/Potential for Microbial Overgrowth

Use of AMZEEQ may result in overgrowth of non-susceptible organisms, including fungi. If superinfection occurs, discontinue AMZEEQ and institute appropriate therapy.

6 ADVERSE REACTIONS

6.1 Clinical Trials Experience

Because clinical trials are conducted under widely varying conditions, adverse reaction rates observed in the clinical trials of a drug cannot be directly compared to rates in the clinical trials of another drug and may not reflect the rates observed in practice.

In 3 randomized, double-blind, vehicle-controlled trials, subjects age 9 years and older applied AMZEEQ or vehicle once daily for 12 weeks. A total of 1,356 subjects were treated with AMZEEQ and 1,058 with vehicle. The majority of subjects were White (74%) and female (60%). Approximately 34% were Hispanic/Latino and 49% were younger than 18 years of age.

The most common adverse reaction reported by ≥1% of subjects treated with AMZEEQ and more frequently than in subjects treated with vehicle was headache, which was reported in 3% of subjects treated with AMZEEQ and 2% of subjects treated with vehicle.

Local tolerability evaluations were conducted at each study visit in the clinical trial by assessment of erythema, dryness, hyperpigmentation, skin peeling and itching. Table 1presents the active assessment of the signs and symptoms of local facial tolerability at Week 12 in subjects treated with AMZEEQ.

Local tolerability signs and symptoms occurred in similar frequency and severity as subjects treated with the vehicle component of AMZEEQ.

Table 1: Facial Cutaneous Tolerability Assessment
 | AMZEEQ, %; (N=1,377)
Symptom/Severity | Mild | Moderate | Severe
Erythema | 14.2 | 1.5 | 0
Dryness | 6.8 | 0.6 | 0
Hyperpigmentation [Hyperpigmentation was most frequently assessed as characteristic of inflammatory and post-inflammatory changes associated with acne.] | 12.4 | 2.8 | 0.1
Skin Peeling | 3.2 | 0.2 | 0
Itching | 5.1 | 0.8 | 0.1

In a 40-week open-label extension safety study (for a total of up to 52 weeks of treatment), frequency and severity of local tolerability signs and symptoms at Week 52 were comparable to those reported at Week 12.

7 DRUG INTERACTIONS

7.1 Anticoagulants

Because tetracyclines have been shown to depress plasma prothrombin activity, patients who are on anticoagulant therapy may require downward adjustment of their anticoagulant dosage.

7.2 Penicillin

Since bacteriostatic drugs may interfere with the bactericidal action of penicillin, it is advisable to avoid giving tetracycline-class drugs in conjunction with penicillin.

7.3 Drug/Laboratory Test Interactions

False elevations of urinary catecholamine levels may occur due to interference with the fluorescence test.

8 USE IN SPECIFIC POPULATIONS

8.1 Pregnancy

Risk Summary

Available data with AMZEEQ use in pregnant women are insufficient to evaluate for a drug-associated risk of major birth defects, miscarriage or other adverse maternal or fetal outcomes. Systemic absorption of AMZEEQ in humans is low following once daily topical administration of AMZEEQ for 21 days [see Clinical Pharmacology (12.3)] . Because of low systemic exposure, it is not expected that maternal use of AMZEEQ will result in significant fetal exposure to the drug.

Tetracycline-class drugs may cause permanent discoloration of teeth and reversible inhibition of bone growth when administered orally during pregnancy [see Warnings and Precautions (5.2, 5.3, 5.4) and Use in Specific Populations (8.4)] .

Animal reproduction studies were not conducted with AMZEEQ. In animal reproduction studies, oral administration of minocycline administered to pregnant rats and rabbits during the period of organogenesis induced skeletal malformations in fetuses at systemic exposures of 750 and 500 times, respectively, the maximum recommended human dose (MRHD; based on AUC comparison) of AMZEEQ (see Data).

The estimated background risk of major birth defects and miscarriage for the indicated population is unknown. All pregnancies have a background risk of birth defect, loss, or other adverse outcomes. In the U.S. general population, the estimated background risk of major birth defects and miscarriage in clinically recognized pregnancies is 2-4% and 15-20%, respectively.

Data

Animal Data

Results of animal studies indicate that tetracyclines cross the placenta, are found in fetal tissues, and can cause retardation of skeletal development of the developing fetus [ see Warnings and Precautions (5.2) ].

Minocycline induced skeletal malformations (bent limb bones) in fetuses when orally administered to pregnant rats and rabbits during the period of organogenesis at doses of 30 mg/kg/day and 100 mg/kg/day, respectively, (750 and 500 times, respectively, the systemic exposure at the MRHD based on AUC comparison). Reduced mean fetal body weight was observed when minocycline was orally administered to pregnant rats during the period of organogenesis at a dose of 10 mg/kg/day (250 times the systemic exposure at the MRHD based on AUC comparison).

Minocycline was assessed for effects on peri- and post-natal development of rats in a study that involved oral administration to pregnant rats during the period of organogenesis through lactation, at doses of 5, 10, or 50 mg/kg/day. In this study, body weight gain was significantly reduced in pregnant females that received 50 mg/kg/day (650 times the systemic exposure at the MRHD based on AUC comparison). No effects of treatment on the duration of the gestation period or the number of live pups born per litter were observed. Gross external anomalies observed in F1 pups (offspring of animals that received oral minocycline) included reduced body size, improperly rotated forelimbs, and reduced size of extremities. No effects were observed on the physical development, behavior, learning ability, or reproduction of F1 pups, and there was no effect on gross appearance of F2 pups (offspring of F1 animals).

8.2 Lactation

Risk Summary

Tetracycline-class drugs, including minocycline, are present in breast milk following oral administration. It is not known whether minocycline is present in human milk after topical administration to the nursing mother. There are no data on the effects of minocycline on milk production. Because of the potential for serious adverse reactions, advise patients that breastfeeding is not recommended during treatment with AMZEEQ [see Warnings and Precautions (5.2)].

8.4 Pediatric Use

The safety and effectiveness of AMZEEQ have been established in pediatric patients 9 years of age and older for the treatment of inflammatory lesions of non-nodular moderate to severe acne vulgaris. Use of AMZEEQ for this indication is supported by three adequate and well controlled 12-week trials in patients 9 years of age and older; two of the trials included a 40-week open-label extension. Additional data was obtained from a 7-day open-label safety and pharmacokinetics study conducted in 20 patients 10 years to less than 17 years of age with acne vulgaris [see Clinical Pharmacology (12.3) and Clinical Studies (14)] . A total of 686 subjects 9 years of age and older received AMZEEQ in these clinical trials.

Safety and effectiveness for this indication have not been established in pediatric patients less than 9 years of age. The use of oral tetracycline drugs during tooth development below the age of 8 years may cause permanent discoloration of the teeth (yellow-gray-brown) and inhibition of bone growth [see Warnings and Precautions (5.2, 5.3)] .

8.5 Geriatric Use

Clinical studies of AMZEEQ did not include sufficient numbers of subjects aged 65 years and over to determine whether they respond differently from younger subjects. Other reported clinical experience has not identified differences in responses between the elderly and younger patients.

11 DESCRIPTION

Minocycline hydrochloride, a semi-synthetic derivative of tetracycline, is [4S‑ (4α,4aα,5aα,12aα)]-4,7-Bis(dimethylamino)-1,4,4a,5,5a,6,11,12a-octahydro-3,10,12,12a‑ tetrahydroxy-1,11-dioxo-2-naphthacenecarboxamide mono hydrochloride. The structural formula is represented below:

C23H27N3O7•HCl M. W. 493.94

Each gram of AMZEEQ contains micronized minocycline 40 mg equivalent to 43 mg minocycline hydrochloride in a yellow suspension foam.

In addition, the 4% AMZEEQ topical foam contains the following inactive ingredients: soybean oil, coconut oil, light mineral oil, cyclomethicone, cetostearyl alcohol, stearic acid, myristyl alcohol, hydrogenated castor oil, white wax (beeswax), stearyl alcohol, docosanol. AMZEEQ topical foam is dispensed from an aluminum container (can) pressurized with propellant (butane + isobutane + propane).

12 CLINICAL PHARMACOLOGY

12.1 Mechanism of Action

The mechanism of action of AMZEEQ for the treatment of acne is unknown.

12.2 Pharmacodynamics

The pharmacodynamics of AMZEEQ for the treatment of acne are unknown.

12.3 Pharmacokinetics

In a pharmacokinetic study, male and female subjects 18 years of age or older with acne vulgaris (N=30) applied approximately 4 grams of AMZEEQ topically to the face, neck, upper chest, upper back, shoulder and upper arms once daily for 21 days. The mean ± SD Cmaxand AUC0-24hwere 1.3 ± 0.6 ng/mL and 23.0 ± 10.8 ng·h/mL, respectively at Day 21 for AMZEEQ. After daily application of AMZEEQ in subjects with acne for 21 days, steady-state was reached by Day 6 and systemic accumulation of minocycline was not evident.

Specific Populations

Age: Pediatric Population

Pharmacokinetics of minocycline was evaluated in 20 subjects 10 years to less than 17 years of age with acne vulgaris following application of approximately 4 grams of AMZEEQ topically to the face, neck, upper chest, upper back, shoulder and upper arms once daily for 7 days. Minocycline was detected in all samples obtained on Day 7. Pharmacokinetic results are presented by age group in Table 2. The overall pediatric population showed 2.4-fold and 2.7-fold higher Cmaxand AUC0-24hcompared to the adult population.

Table 2: Clinical Pharmacokinetics of Minocycline when treated with AMZEEQ (~4 g) in Pediatric Subjects Aged 10 to <17 years with Acne Vulgaris
Age Group (years) | Mean ± SD Cmax (ng/mL) | Mean ± SD AUC0-24h(ng·h/mL)
10 - 11 | 4.5 ± 4.0 | 90.9 ± 90.2
12 - 14 | 2.8 ± 2.2 | 54.0 ± 46.2
15 - <17 | 2.0 ± 1.2 | 40.8 ± 23.8
10 - <17 | 3.1 ± 2.7 | 61.1 ± 59.2

12.4 Microbiology

Resistance

Propionibacterium acnesstrains displayed a low propensity for the development of resistance to minocycline, with spontaneous mutation frequencies being <10^−8at 2 to 16 × MIC.

Antimicrobial Activity

Minocycline is active in vitro against most isolates of Propionibacterium acnes; however, the clinical significance is unknown.

13 NONCLINICAL TOXICOLOGY

13.1 Carcinogenesis, Mutagenesis, Impairment of Fertility

In a carcinogenicity study in which minocycline hydrochloride was orally administered to male and female rats once daily for up to 104 weeks at dosages up to 200 mg/kg/day, minocycline hydrochloride was associated in both sexes with follicular cell tumors of the thyroid gland, including increased incidences of adenomas, carcinomas and the combined incidence of adenomas and carcinomas in males, and adenomas and the combined incidence of adenomas and carcinomas in females. In a carcinogenicity study in which minocycline hydrochloride was orally administered to male and female mice once daily for up to 104 weeks at dosages up to 150 mg/kg/day, exposure to minocycline hydrochloride did not result in a significantly increased incidence of neoplasms in either males or females.

Minocycline was not mutagenic in vitro in a bacterial reverse mutation assay (Ames test) or CHO/HGPRT mammalian cell assay in the presence or absence of metabolic activation. Minocycline was not clastogenic in vitro using human peripheral blood lymphocytes or in vivo in a mouse micronucleus test.

Male and female reproductive performance in rats was unaffected by oral doses of minocycline of up to 300 mg/kg/day (10,000 times the systemic exposure at the MRHD based on AUC comparison). However, oral administration of 100 or 300 mg/kg/day of minocycline to male rats (3,800 or 10,000 times, respectively, the systemic exposure at the MRHD based on AUC comparison), adversely affected spermatogenesis.

Effects observed at 300 mg/kg/day of oral minocycline included a reduced number of sperm cells per gram of epididymis, an apparent reduction in the percentage of sperm that were motile, and (at 100 and 300 mg/kg/day) increased numbers of morphologically abnormal sperm cells. Morphological abnormalities observed in sperm samples included absent heads, misshapen heads, and abnormal flagella.

14 CLINICAL STUDIES

The safety and efficacy of AMZEEQ was assessed in three 12-week, multicenter, randomized, double-blind, vehicle-controlled studies (Study 1 [NCT02815267], Study 2 [NCT02815280], and Study 3 [NCT03271021]) in subjects with moderate to severe acne vulgaris. Efficacy was assessed in a total of 2,418 subjects 9 years of age and older. AMZEEQ or its vehicle were applied once daily for 12 weeks; no other topical or systemic medication affecting the course of acne vulgaris was permitted for use during these studies.

Subjects were required to have an inflammatory and non-inflammatory lesion count in the range 20-50 lesions and 25-100 lesions respectively, and an Investigator Global Assessment (IGA) score of 3 (“moderate”) or 4 (“severe”) at baseline.

Overall, 74% were Caucasian and 61% were female. Forty-two (2%) subjects were 9 to 11 years of age, 1,139 (47%) subjects were 12 to 17 years of age, and 1,237 (51%) subjects were 18 years or older. At baseline, subjects had a mean inflammatory lesion count of 31.2 and a mean non-inflammatory lesion count of 49.3. Additionally, approximately 85% of subjects had an IGA score of 3 (“moderate”).

The co-primary efficacy endpoints were the absolute change from baseline in inflammatory lesion counts at Week 12 and the proportion of subjects with treatment success at Week 12, defined as an IGA score of 0 (“clear”) or 1 (“almost clear”), and at least a two-grade improvement (decrease) from baseline at Week 12. The efficacy results are presented in Table 3.

Table 3: Clinical Efficacy of AMZEEQ in Subjects with Acne Vulgaris at Week 12
 | Study 1 |  | Study 2 |  | Study 3
 | AMZEEQ (N=307) | Vehicle (N=159) | AMZEEQ; (N=312) | Vehicle; (N=152) | AMZEEQ; (N=738) | Vehicle; (N=750)
IGA
Treatment Successa | 8.1% | 4.8% | 15.8% | 8.4% | 30.8% | 19.6%
Difference from Vehicle; (95% CI) | 3.3%; (-1.5%, 8.2%) |  | 7.4%; (0%, 13.7%) |  | 11.2%; (6.6%, 15.8%)
Inflammatory Lesion Count
MeanbAbsolute Change from Baseline | -14.0 | -11.2 | -13.7 | -10.5 | -16.4 | -12.7
Difference from Vehicle; (95% CI) | -2.8; (-4.9, -0.7) |  | -3.2; (-5.6, -0.9) |  | -3.7; (-4.8, -2.5)
MeanbPercent Change from Baseline | -44% | -34% | -43% | -34% | -54% | -42%
Difference from Vehicle; (95% CI) | -10%; (-17%, -3%) |  | -10%; (-17%, -2%) |  | -12%; (-16%, -8%)
aTreatment success is defined as an IGA score of 0 (“clear”) or 1 (“almost clear”), and at least a two-grade improvement (decrease) from baseline.
bMeans presented in table are Least Square (LS) means.

16 HOW SUPPLIED/STORAGE AND HANDLING

How Supplied

AMZEEQ®(minocycline) topical foam, 4% is a yellow suspension supplied in a pressurized aluminum aerosol container (can). Each gram of AMZEEQ contains 40 mg of minocycline equivalent to 43 mg of minocycline hydrochloride, and is supplied as follows:

NDC 69489-201-30 30 g Can

Storage

AMZEEQ must be stored at 2ºC - 8ºC (36ºF - 46ºF) until dispensed to the patient.

Once dispensed, the patient is to store AMZEEQ at room temperature below 25ºC (77ºF) for 90 days. Do not store in the refrigerator.

Handling

Allow the can to warm to room temperature before first use.

Shake can well before use.

WARNING: Flammable. Avoid fire, flame, or smoking during and immediately following application. Contents under pressure. Do not puncture or incinerate. Do not expose to heat or temperatures above 49oC (120oF).

17 PATIENT COUNSELING INFORMATION

Advise the patient to read the FDA-approved patient labeling (Patient Information and Instructions for Use).

Inform patients using AMZEEQ (minocycline) topical foam, 4% of the following information and instructions:

Flammability

The propellant in AMZEEQ is flammable. Instruct the patient to avoid fire, flame, and smoking during and immediately following application.

Tooth Discoloration

Advise caregivers of pediatric patients that AMZEEQ may cause permanent discoloration of deciduous and permanent teeth during tooth development (generally up to the age of 8 years) based on observations with oral tetracycline.

Lactation

Advise women that breastfeeding is not recommended during AMZEEQ therapy.

Tissue Hyperpigmentation

Inform patients that AMZEEQ may cause discoloration of skin, scars, teeth or gums based on observations with oral minocycline.

Clostridioides difficileAssociated Diarrhea

Advise patients that Clostridioides difficileassociated diarrhea can occur with oral minocycline therapy. Advise patients to seek medical attention if they develop watery or bloody stools while using AMZEEQ.

Hepatotoxicity

Inform patients about the possibility of hepatotoxicity reported with oral minocycline. Advise patients to seek medical advice if they experience symptoms or signs of hepatotoxicity, including loss of appetite, tiredness, diarrhea, jaundice, increased bleeding tendencies, confusion, and sleepiness.

Central Nervous System Effects

Inform patients that central nervous system adverse reactions including dizziness or vertigo have been reported with oral minocycline therapy. Caution patients about driving vehicles or using hazardous machinery if they experience such symptoms while on AMZEEQ.

Intracranial Hypertension

Inform patients that intracranial hypertension can occur with minocycline therapy. Advise patients to seek medical attention if they develop unusual headache, visual symptoms, such as blurred vision, diplopia, and vision loss.

Photosensitivity

Inform patients that photosensitivity manifested by an exaggerated sunburn reaction has been observed in some individuals taking oral tetracyclines, including minocycline. Advise patients to minimize or avoid exposure to natural or artificial UV light (tanning beds or UVA/B treatment) while using AMZEEQ. Discuss other sun protection measures, if patients need to be outdoors while using AMZEEQ. Advise patients to discontinue treatment at the first evidence of sunburn.

Autoimmune Syndromes

Inform patients that autoimmune syndromes, including drug-induced lupus-like syndrome, autoimmune hepatitis, vasculitis and serum sickness have been observed with oral tetracycline-class drugs, including minocycline. Symptoms may be manifested by arthralgia, fever, rash and malaise. Advise patients who experience such symptoms to stop the drug immediately and seek medical help.

Other Information

AMZEEQ should be applied exactly as directed.

AMZEEQ may stain fabric.

Manufactured by: ASM Aerosol-Service AG, Mohlin, Switzerland
Manufactured for: Journey Medical Corporation, Scottsdale, AZ 85258
Product of Portugal or Italy

AMZ-P01-R01

AMZEEQ is a registered trademark of Journey Medical Corporation
All other trademarks are the properties of their respective owners.
Copyright © 2023 Journey Medical Corporation. All rights reserved.

PATIENT INFORMATION

AMZEEQ®(am-Zeek)

(minocycline)

topical foam

Important Information: AMZEEQ is for use on skin only (topical use). AMZEEQ is not for use in your mouth, eyes or vagina.

What is AMZEEQ?

AMZEEQ is a prescription medicine used on the skin (topical) for the treatment of pimples and red bumps (non-nodular inflammatory lesions) that happen with moderate to severe acne vulgaris in adults and children 9 years of age and older.

AMZEEQ should not be used for the treatment of infections.

It is not known if AMZEEQ is safe and effective in children under 9 years of age.

Do not use AMZEEQif you are allergic to any tetracycline medicines or to any of the ingredients in AMZEEQ. Ask your healthcare provider or pharmacist for a list of these medicines if you are not sure.

What should I tell my healthcare provider before using AMZEEQ?

Before using AMZEEQ, tell your healthcare provider about all of your medical conditions, including if you:

• have diarrhea or watery stools

• have liver problems

• have kidney problems

• are pregnant or plan to become pregnant. Taking tetracycline medicines by mouth during pregnancy may cause serious side effects on the growth of bone and teeth of your baby. AMZEEQ topical foam is used on your skin and it is not known if it will harm your unborn baby.•are breastfeeding or plan to breastfeed. Do not breastfeed during treatment with AMZEEQ.

Tell your healthcare provider about all the other medicines you take,including prescription and over-the-counter medicines, vitamins and herbal supplements. Tetracycline medicines taken by mouth may affect the way other medicines work, and may increase your risk of certain side effects.

Especially tell your healthcare provider if you take:

• a blood thinner medicine.

• a penicillin antibiotic medicine

• isotretinoin

Ask your healthcare provider or pharmacist if you are not sure if your medicine is one that is listed above. Know the medicines you take. Keep a list of them to show your healthcare provider and pharmacist.

How should I use AMZEEQ?

• See the detailed “Instructions for Use”included with this leaflet for directions about how to apply AMZEEQ the right way.

• Use AMZEEQ exactly as your healthcare provider tells you.

• Apply AMZEEQ to the affected skin area(s) at about the same time each day, at least 1 hour before bedtime.

• Do not bathe, shower, or swim for at least 1 hour after applying AMZEEQ.

• Wash your hands after applying AMZEEQ.

What should I avoid while using AMZEEQ?

• AMZEEQ is flammable. Avoid fire, flame, and smoking when applying and right after you apply AMZEEQ.

• Limit your time in sunlight. Avoid sunlight or artificial sunlight such as sunlamps or tanning beds. Use sun protection measures such as sunscreen and wear loose-fitting clothes that cover your skin while out in sunlight. Stop using AMZEEQ if you get sunburn.

• Minocycline taken by mouth may cause feelings of light-headedness, dizziness, or spinning (vertigo). You should not drive or operate dangerous machinery if you have these symptoms during treatment with AMZEEQ.

What are possible side effects of AMZEEQ?

AMZEEQ contains minocycline, a tetracycline medicine. Tetracyclines, when taken by mouth, may cause serious side effects, including:

• Harm to an unborn baby.See “What should I tell myhealthcare provider before using AMZEEQ?”

• Permanent tooth discoloration.Tetracycline medicine when taken by mouth may permanently turn a baby or child's teeth yellow-gray-brown during tooth development. You should not use AMZEEQ during tooth development. Tooth development happens in the second and third trimesters of pregnancy, and from birth up to 8 years of age.

• Slow bone growth.Tetracycline medicine taken by mouth may slow bone growth in infants and children. Slow bone growth is reversible after stopping treatment.

• Diarrhea.Diarrhea can happen with most antibiotics, including minocycline taken by mouth. This diarrhea may be caused by an infection (Clostridioides difficile)in your intestines. Call your healthcare provider right away if you get watery or bloody stools while using AMZEEQ.

• Liver problems.Minocycline taken by mouth to treat acne can cause serious liver problems that may lead to death. Stop using AMZEEQ and call your healthcare provider right away if you get any of the following signs or symptoms of liver problems:

o loss of appetite

o tiredness

o diarrhea

o yellowing of your skin or the white of your eyes (jaundice)

o bleeding more easily than normal

o confusion

o sleepiness

• Central nervous system effects.See “ What should I avoid while using AMZEEQ?”

• Increased pressure in the brain (intracranial hypertension). This condition may lead to vision changes and permanent vision loss. You are more likely to get intracranial hypertension if you are a female of childbearing potential and are overweight or have a history of intracranial hypertension. Stop using AMZEEQ and tell your healthcare provider right away if you have blurred vision, double vision, vision loss, or unusual headaches.

• Immune system reactions including a lupus-like syndrome, hepatitis, and inflammation of blood or lymph vessels (vasculitis)have happened during treatment with minocycline taken by mouth .Call your healthcare provider right away if you get a fever, rash, joint pain, or body weakness.

• Sensitivity to sunlight (photosensitivity).See “What should I avoid while using AMZEEQ?”

• Serious skin or allergic reactionshave happened during treatment with minocycline taken by mouth that may affect parts of your body such as your liver, lungs, kidneys and heart. Sometimes these can lead to death. Stop using AMZEEQ and go to the nearest hospital emergency room right away if you have any of the following signs or symptoms:

o skin rash, hives, sores in your mouth, or your skin blisters and peels

o swelling of your face, eyes, lips, tongue, or throat

o trouble swallowing or breathing

o blood in your urine

o fever, yellowing of the skin or the whites of your eyes (jaundice), dark colored urine

o pain on the right side of the stomach area (abdominal pain)

o chest pain or abnormal heartbeats

o swelling in your legs, ankles, and feet

• Discoloration (hyperpigmentation).Minocycline taken by mouth may cause darkening of your skin, scars, teeth, or gums.

The most common side effect of AMZEEQ isheadache.

Your healthcare provider may stop your treatment with AMZEEQ if you develop certain side effects.

These are not all the possible side effects with AMZEEQ.

Call your doctor for medical advice about side effects. You may report side effects to FDA at 1-800-FDA-1088.

How should I store AMZEEQ?

• Store AMZEEQ at room temperature below 77ºF (25ºC) for 90 days.

• Do not store AMZEEQ in the refrigerator.

• Do not puncture or burn the AMZEEQ can.

• Do not expose to heat or temperatures above 120ºF (49ºC)

Keep AMZEEQ and all medicines out of the reach of children.

General information about the safe and effective use of AMZEEQ.

Medicines are sometimes prescribed for purposes other than those listed in a Patient Information leaflet. Do not use AMZEEQ for a condition for which it was not prescribed. Do not give AMZEEQ to other people, even if they have the same symptoms you have. It may harm them. You can ask your healthcare provider or pharmacist for information about AMZEEQ that is written for health professionals.

What are the ingredients in AMZEEQ?

Active ingredient:minocycline

Inactive ingredients:soybean oil, coconut oil, light mineral oil, cyclomethicone, cetostearyl alcohol, stearic acid, myristyl alcohol, hydrogenated castor oil, white wax (beeswax), stearyl alcohol, docosanol and propellant (butane + isobutane + propane).
Manufactured by: ASM Aerosol-Service AG, Mohlin, Switzerland

Manufactured for: Journey Medical Corporation, Scottsdale, AZ 85258

Product of Portugal or Italy
AMZ-P02-R01
AMZEEQ is a registered trademark of Journey Medical Corporation.
All other trademarks are the properties of their respective owners.
Copyright © 2023, Journey Medical Corporation. All rights reserved.
For more information, go to www.AMZEEQ.com or call Journey Medical Corporation at 1-855-531-1859.

This Patient Information has been approved by the U.S. Food and Drug Administration. Issued: 10/2023

INSTRUCTIONS FOR USE
AMZEEQ®(am-Zeek)
(minocycline)
topical foam

Important Information:AMZEEQ is for use on skin only (topical use). AMZEEQ is not for use in your mouth, eyes or vagina.

Read this Instructions for Use before you start using AMZEEQ and each time you get a refill. There may be new information. This information does not take the place of talking with your healthcare provider about your medical condition or treatment. Use AMZEEQ exactly as your healthcare provider tells you.

Before applying AMZEEQ:

• Allow the AMZEEQ can to warm to room temperature before first use.

• Wash your face gently with mild cleanser, rinse with water, and pat your skin dry.

Step 1:Shake the can well. Place thumb under tab above nozzle and lift up to remove the cap from the AMZEEQ foam can.

Step 2:Press the top of the can to dispense a small amount of AMZEEQ foam onto your fingertips.

Step 3:Apply and gently rub AMZEEQ foam into the affected areas.

Step 4:If acne is present on other parts of your body (neck, shoulders, arms, back or chest), additional amounts of AMZEEQ foam should also be applied to these affected areas as directed by your healthcare provider.

•Wash your hands after applying AMZEEQ.•AMZEEQ can stain fabric.

This Instructions for Use has been approved by the U.S. Food and Drug Administration. Issued: 10/2023

Manufactured by: ASM Aerosol-Service AG, Mohlin, Switzerland
Manufactured for: Journey Medical Corporation, Scottsdale, AZ 85258
Product of Portugal or Italy
AMZ-P03-R01

AMZEEQ is a registered trademark of Journey Medical Corporation.
All other trademarks are the properties of their respective owners.

Copyright © 2023, Journey Medical Corporation. All rights reserved.

PACKAGE/LABEL PRINCIPAL DISPLAY PANEL - 30g Trade (69489-201-30)

AMZEEQ Trade Label

NDC 69489- 201-30 - Label

amzeeq®

(minocycline)
topical foam, 4%

For topical use only, not for oral, ophthalmic or intravaginal use

Rx only

[logo -Journey Medical Corporation]

30 g

NDC 69489- 201-30 - Carton

amzeeq®

(minocycline)
topical foam, 4%

For topical use only,

not for oral, ophthalmic

or intravaginal use

Rx only

[logo -Journey Medical Corporation]

30 g

PACKAGE/LABEL PRINCIPAL DISPLAY PANEL - 3 g Sample (69489-201-03)

AMZEEQ Sample Labels

NDC 69489- 201-03 - Label

Physician Sample Not for Sale

amzeeq®

(minocycline)
topical foam, 4%

For topical use only, not for oral,

ophthalmic or intravaginal use

Rx only

[logo -Journey Medical Corporation]

3 g

NDC 69489- 201-03 - Carton

Physician Sample

Not for Sale

amzeeq®

(minocycline)
topical foam, 4%

For topical use only,

not for oral, ophthalmic

or intravaginal use

Rx only

[logo -Journey Medical Corporation]

3 g